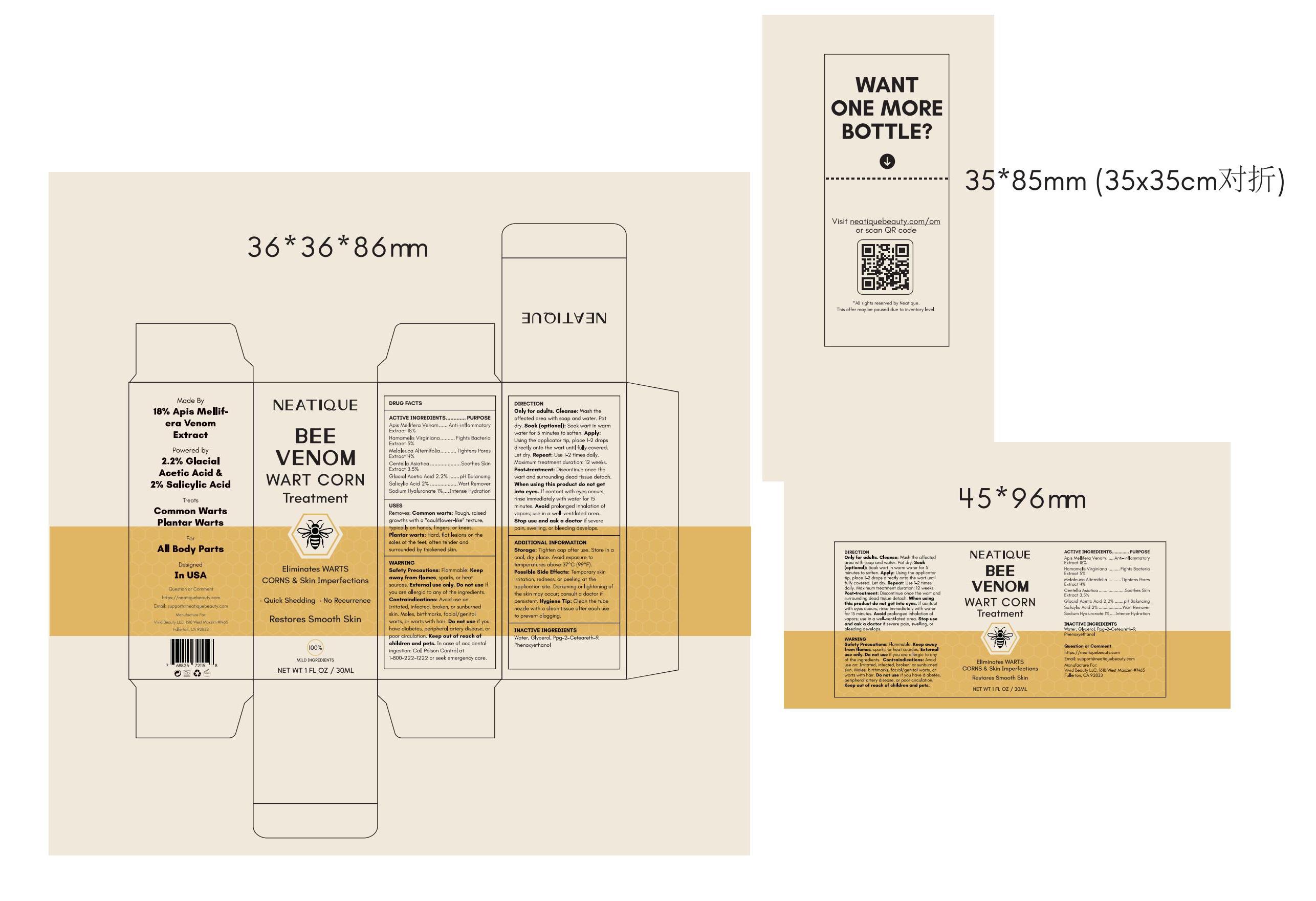 DRUG LABEL: Neatique Bee Venom Wart Corn Treatment Liquid
NDC: 85587-004 | Form: LIQUID
Manufacturer: Shenzhen Zealous Ecommerce Technology Co., Ltd
Category: otc | Type: HUMAN OTC DRUG LABEL
Date: 20250612

ACTIVE INGREDIENTS: CENTELLA ASIATICA TRITERPENOIDS 3.5 g/100 mL; SODIUM HYALURONATE 1 g/100 mL; ACETIC ACID 2.2 g/100 mL; SALICYLIC ACID 2 g/100 mL; APIS MELLIFERA VENOM 18 g/100 mL; MELALEUCA ALTERNIFOLIA LEAF 4 g/100 mL; HAMAMELIS VIRGINIANA ROOT BARK/STEM BARK 5 g/100 mL
INACTIVE INGREDIENTS: WATER; PPG-2-CETEARETH-9; PHENOXYETHANOL; GLYCERIN

85587-004

Active Ingredient

Apis Mellifera Venom Extract 18%
Hamamelis Virginiana Extract 5%
Melaleuca Alternifolia Extract 4%
Centella Asiatica Extract 3.5%
Glacial Acetic Acid 2.2%
Salicylic Acid 2%
Sodium Hyaluronate 1%

Purpose

Apis Mellifera Venom Extract 18% - Anti-inflammatory
Hamamelis Virginiana Extract 5% - Fights Bacteria
Melaleuca Alternifolia Extract 4% - Tightens Pores
Centella Asiatica Extract 3.5% - Soothes Skin
Glacial Acetic Acid 2.2% - pH Balancing
Salicylic Acid 2% - Wart Remover
Sodium Hyaluronate 1% - Intense Hydration

Use

Removes: Common warts: Rough, raised growths with a "cauliflower-like" texture, typically on hands, fingers, or knees. Plantar warts: Hard, flat lesions on the soles of the feet, often tender and surrounded by thickened skin.

Warnings

Safety Precautions: Flammable: Keep away from flames, sparks, or heat sources. External use only.

Do not use if you are allergic to any of the ingredients. Do not use if you have diabetes, peripheral artery disease, or poor circulation.

When Using

When using this product do not get into eyes.

Stop Use

Stop use and ask a doctor if severe pain, swelling, or bleeding develops.

Ask Doctor

Stop use and ask a doctor if severe pain, swelling, or bleeding develops.

Keep out of reach of children and pets.

Directions

Only for adults. Cleanse: Wash the affected area with soap and water. Pat dry. Soak (optional): Soak wart in warm water for 5 minutes to soften. Apply: Using the applicator tip, place 1–2 drops directly onto the wart until fully covered. Let dry. Repeat: Use 1–2 times daily. Maximum treatment duration: 12 weeks. Post-treatment: Discontinue once the wart and surrounding dead tissue detach.

Other information

Storage: Tighten cap after use. Store in a cool, dry place. Avoid exposure to temperatures above 37°C (99°F). Possible Side Effects: Temporary skin irritation, redness, or peeling at the application site. Darkening or lightening of the skin may occur; consult a doctor if persistent. Hygiene Tip: Clean the tube nozzle with a clean tissue after each use to prevent clogging.

Inactive ingredients

Water, Glycerol, Ppg-2-Ceteareth-9, Phenoxyethanol

Questions

https://neatiquebeauty.com
Email: support@neatiquebeauty.com